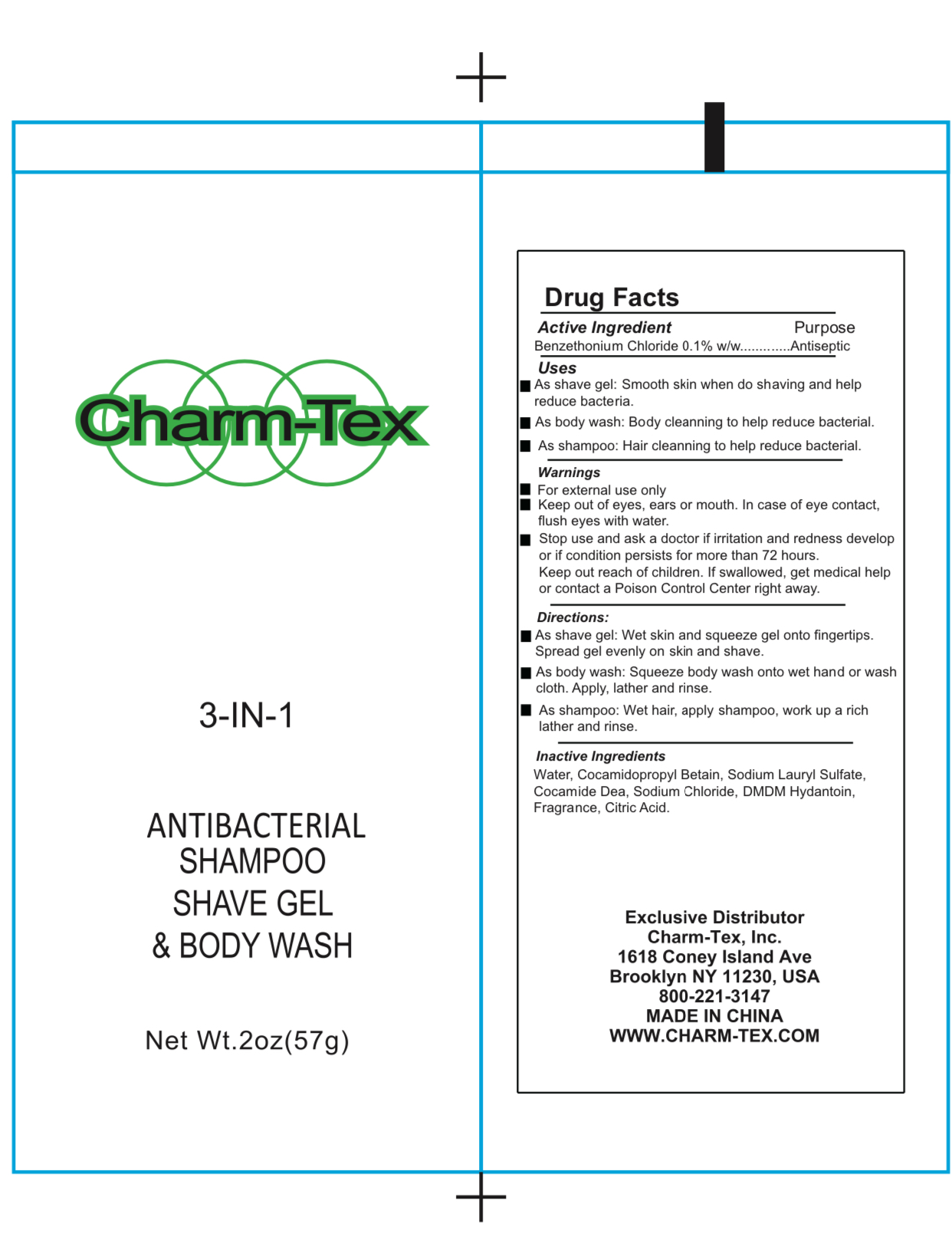 DRUG LABEL: Charm Tex 3 IN 1 Antibacterial Shave Gel Body Wash
NDC: 77573-009 | Form: LOTION/SHAMPOO
Manufacturer: Jiangsu Aimeili Cosmetic Co.,Ltd.
Category: otc | Type: HUMAN OTC DRUG LABEL
Date: 20240105

ACTIVE INGREDIENTS: BENZETHONIUM CHLORIDE 0.1 g/100 g
INACTIVE INGREDIENTS: COCAMIDOPROPYL BETAINE; WATER; SODIUM LAURYL SULFATE; DMDM HYDANTOIN; SODIUM CHLORIDE; CITRIC ACID MONOHYDRATE

77573-009 Charm_Tex 3 in 1

Active Ingredient

Benzethonium Chloride 0.1%

Purpose

Antiseptic

Use

As shaving gel: Smooth skin when do shaving and help reduce bacteria

As body wash: Body cleaning to help reduce bacteria

As shampoo: Hair cleaning to help reduce bacteria

Warnings

For external use only

STOP USE

Keep out of eyes, ears, and mouth. In case of eye contact, flush eyes with water

Stop use and ask a doctor if irritation and redness develop or if condition persists for more than 72 hours

Keep out of reach of children. If swallowed, get medical help or contact a Poison Control Center right away.

Directions

As shave gel: Wet skin and squeeze gel onto figer tips. Spread gel evenly on skin and shave

As body wash: Squeeze body wash onto wet hand or wash cloth. Apply, lather, and rinse.

As shampoo: Wet hair, apply shampoo, work up a rich lather and rinse

Inactive ingredients

Water, Cocamidopropyl Betaine, Sodium Lauryl Sulfate, Cocamide Dea, Sodium Chloride, DMDM Hydantoin, Fragrance, Citric Acid